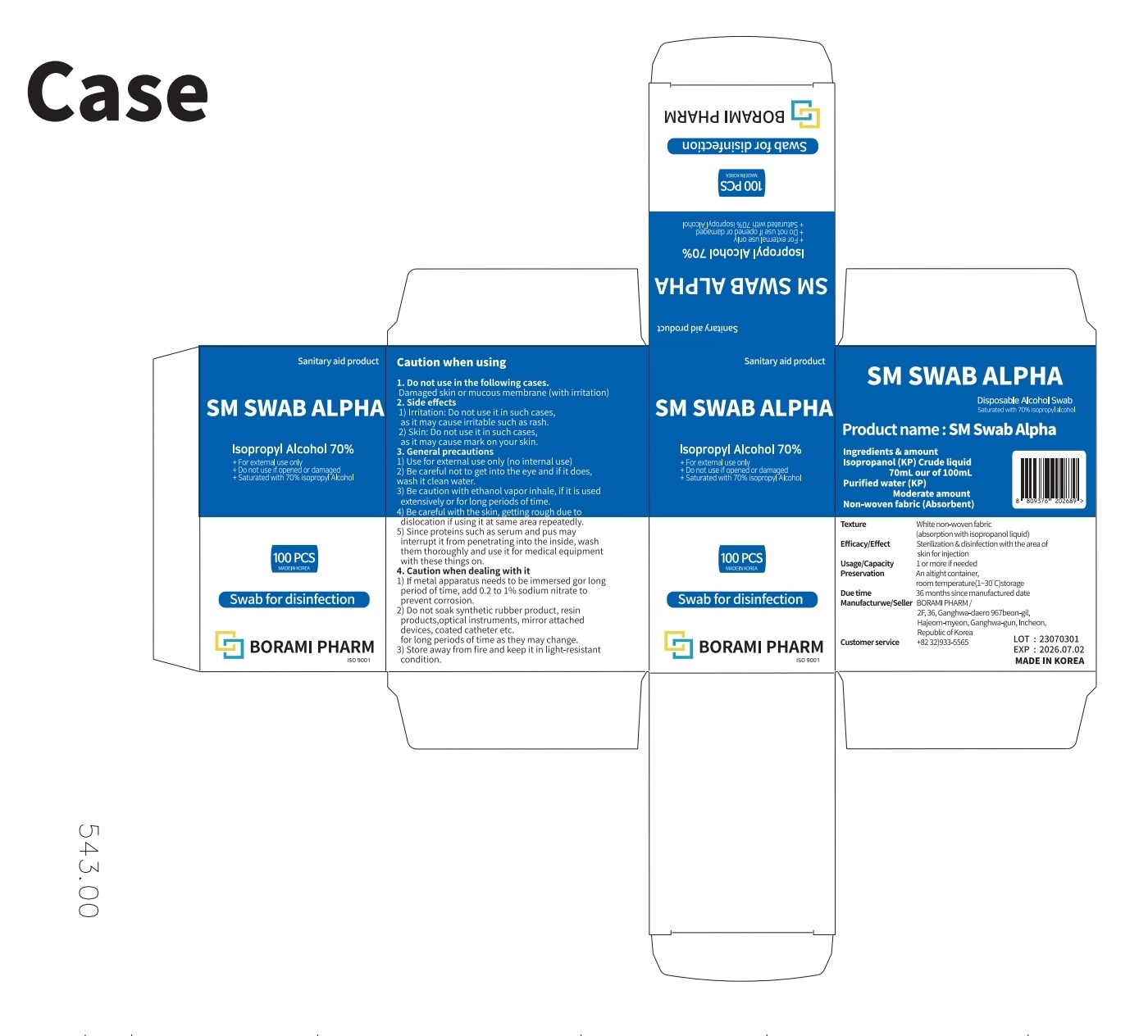 DRUG LABEL: SM SWABALPHA
NDC: 83601-0001 | Form: LIQUID
Manufacturer: Borami
Category: otc | Type: HUMAN OTC DRUG LABEL
Date: 20250210

ACTIVE INGREDIENTS: ISOPROPYL ALCOHOL 70 mL/100 mL
INACTIVE INGREDIENTS: WATER

Drug Facts

ACTIVE INGREDIENT

isopropyl alcohol

PURPOSE

swap for disinfection

KEEP OUT OF REACH OF THE CHILDREN

INDICATIONS AND USAGE

apply a swab to the area of skin for injection for sterilization & disinfection

WARNINGS

■ For external use only.

■ Do not use in eyes.

■ lf swallowed, get medical help promptly.

■ Stop use, ask doctor lf irritation occurs.

■ Keep out of reach of children.

DOSAGE AND ADMINISTRATION

for external use only

INACTIVE INGREDIENT

purified water, non-woven